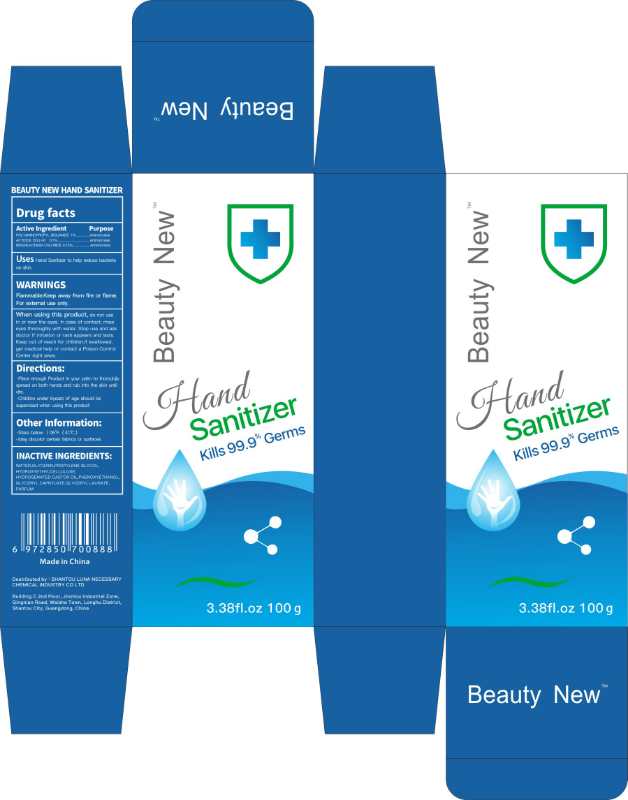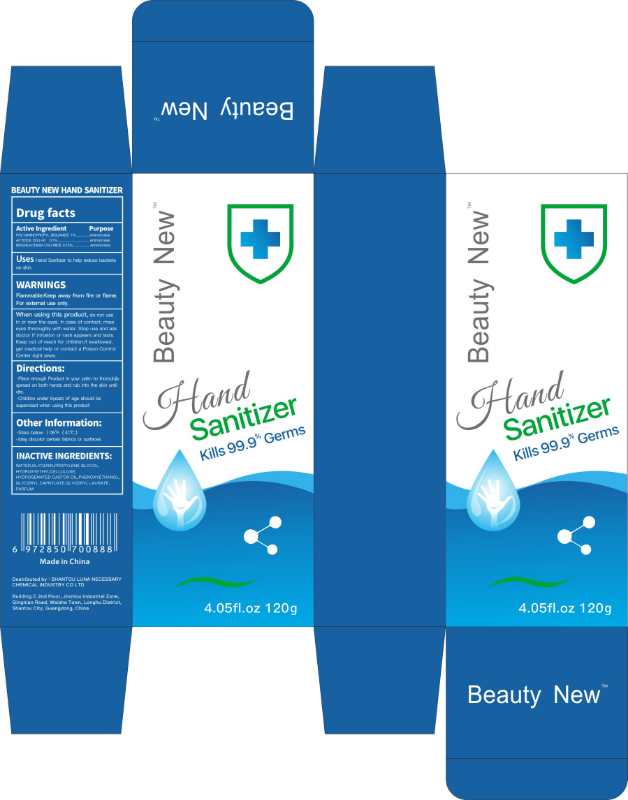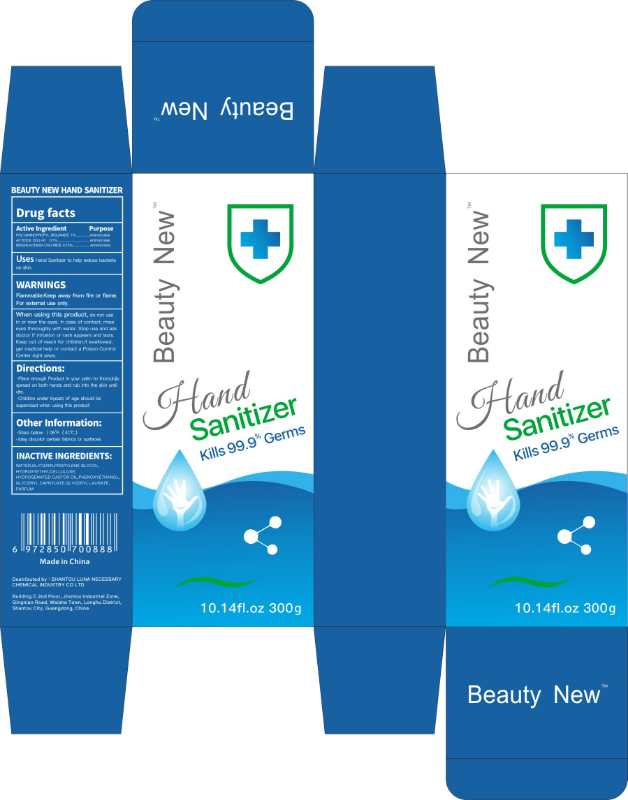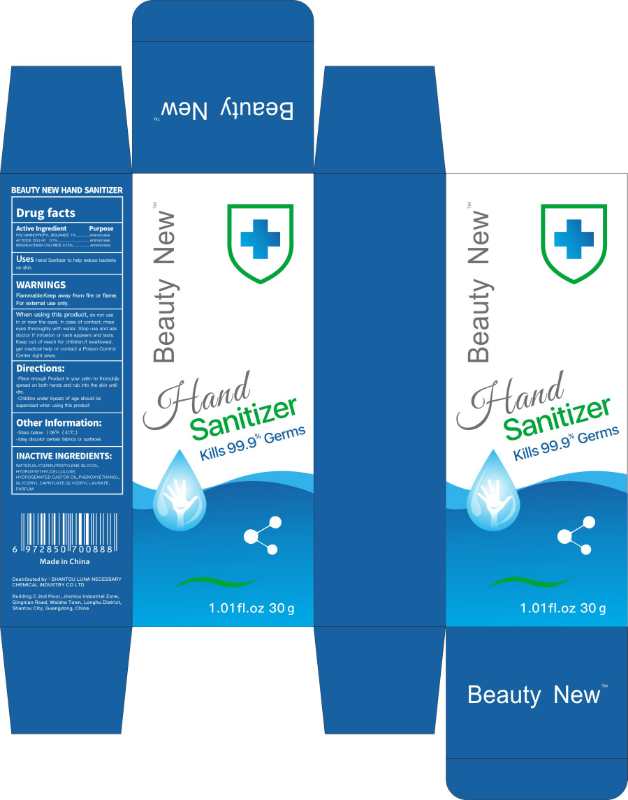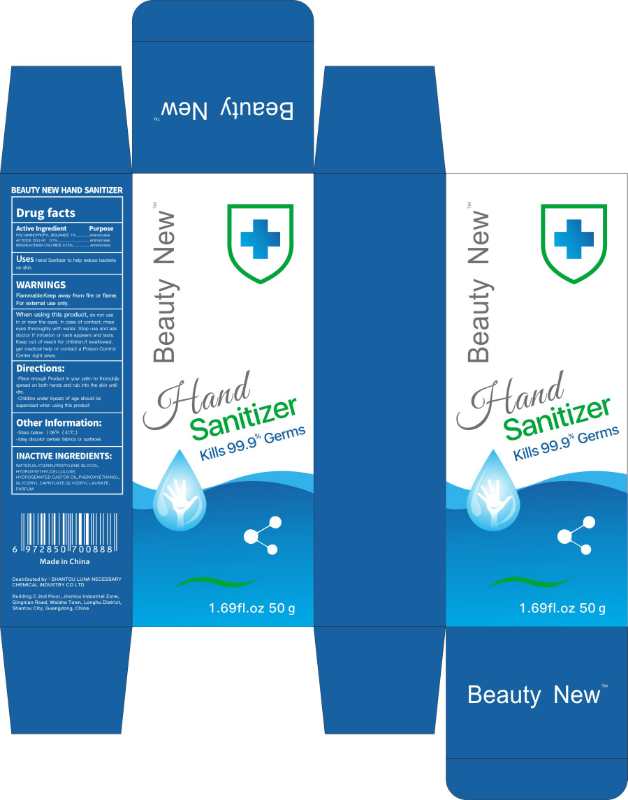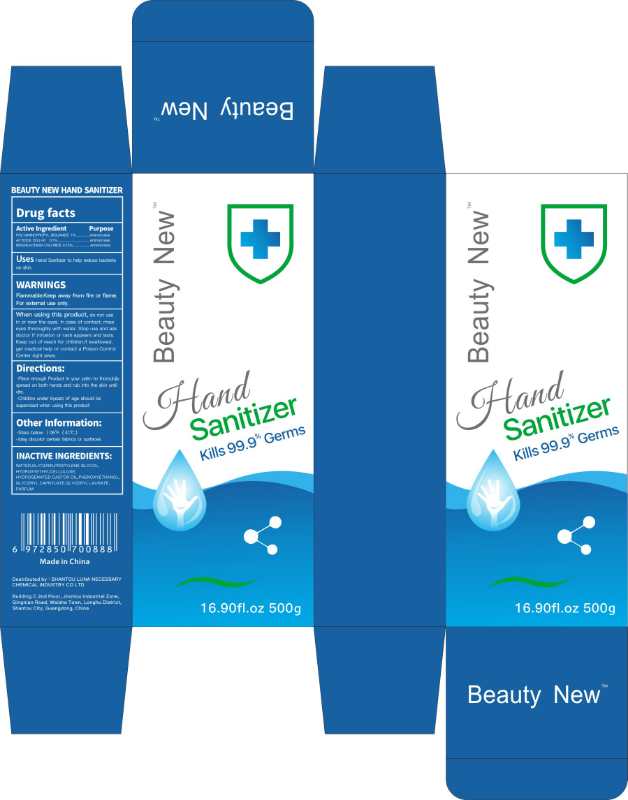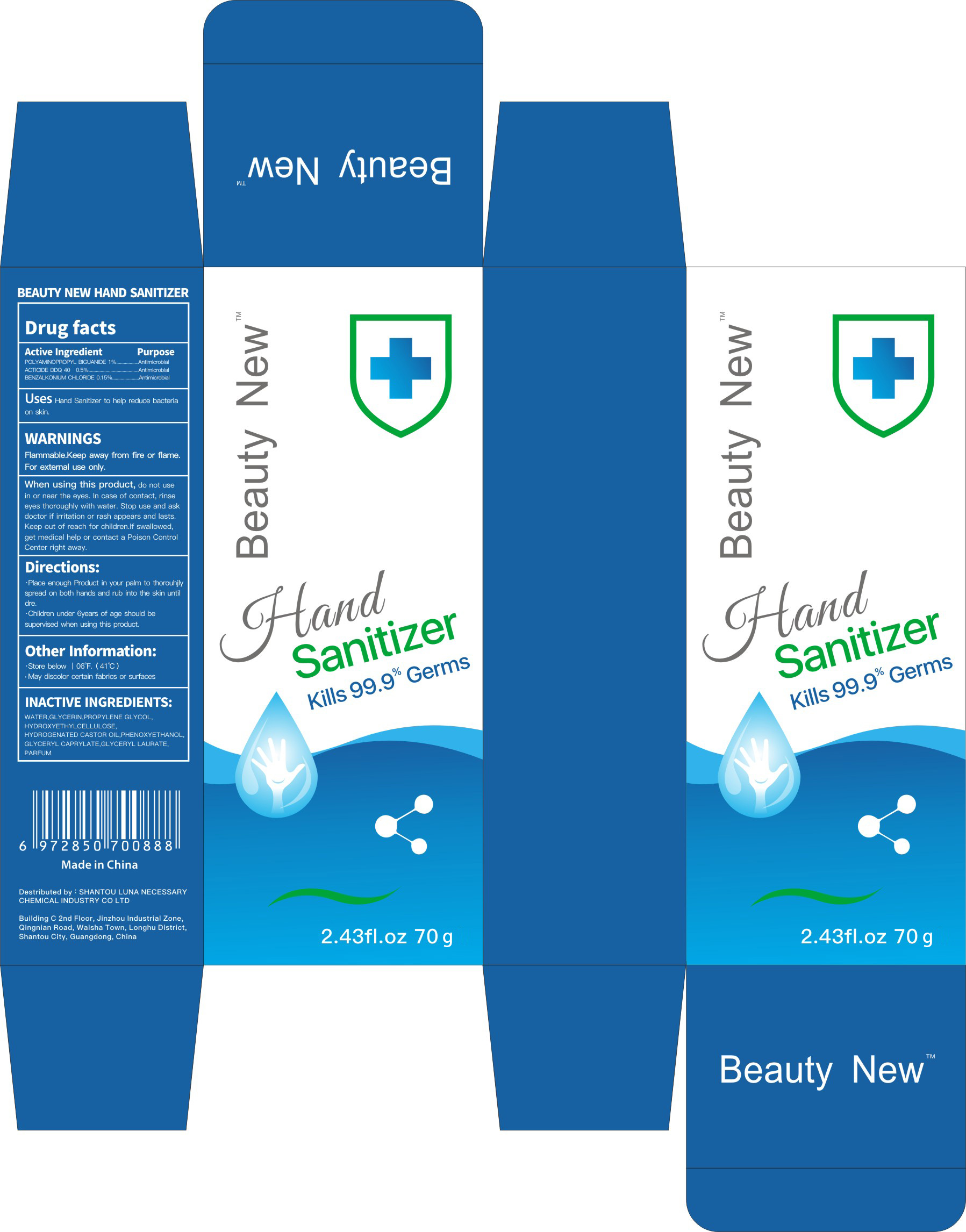 DRUG LABEL: BEAUTY NEW HAND SANITIZER
NDC: 75119-011 | Form: GEL
Manufacturer: SHANTOU LUNA NECESSARY CHEMICAL INDUSTRY CO.,LTD
Category: otc | Type: HUMAN OTC DRUG LABEL
Date: 20200423

ACTIVE INGREDIENTS: DIDECYLDIMONIUM CHLORIDE 0.5 g/100 g; BENZALKONIUM CHLORIDE 0.15 g/100 g; POLYAMINOPROPYL BIGUANIDE 1 g/100 g
INACTIVE INGREDIENTS: GLYCERYL CAPRYLATE; PHENOXYETHANOL; HYDROXYETHYL CELLULOSE, UNSPECIFIED; PROPYLENE GLYCOL; GLYCERIN; WATER; GLYCERYL LAURATE

Uses

antimicrobial

Directions

Place enough Product in your palm to thorouhjly spread on both hands and rub into the skin until dre.

Children under 6years of age should be supervised when using this product.

Warnings

Flammable.Keep away from fire or flame.

For external use only.

When using this product, do not use in or near the eyes. In case of contact, rinse eyes thoroughly with water. Stop use and ask doctor if irritation or rash appears and lasts.Keep out of reach for children.If swallowed, get medical help or contact a Poison Control Center right away.

Other information

- Store below 丨06°F.（41℃）
- May discolor certain fabrics or surfaces

Inactive ingredients

WATER,GLYCERIN,PROPYLENE GLYCOL,

HYDROXYETHYLCELLULOSE,

HYDROGENATED CASTOR OIL

DOSAGE AND ADMINISTRATION

Store below 丨06°F.（41℃）

May discolor certain fabrics or surfaces

KEEP OUT OF REACH OF CHILDREN

Children under 6years of age should be supervised when using this product.

ACTIVE INGREDIENT

2,3-DICHLORO-5,6-DICYANOBENZOQUINONE 0.15%

POLYAMINOPROPYL BIGUANIDE 1%

BENZALKONIUM CHLORIDE 0.15%